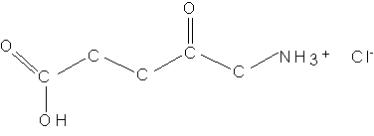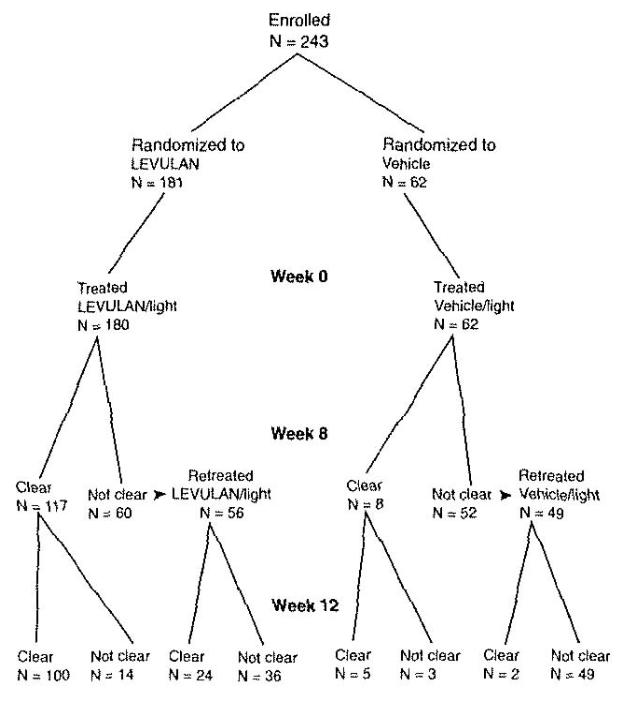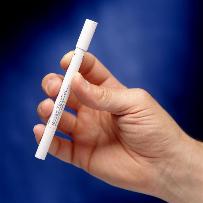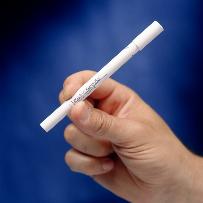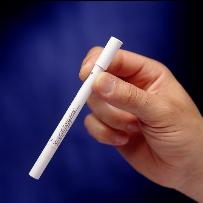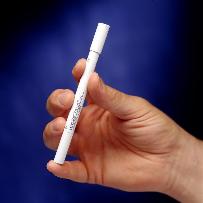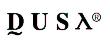 DRUG LABEL: Unknown
Manufacturer: DUSA
Category: prescription | Type: Human Prescription Drug Label
Date: 20061008

Levulan® Kerastick®
(aminolevulinic acid HCl) for Topical Solution, 20%
For Topical Use Only
Not for Opthalmic Use

DESCRIPTION

LEVULAN® KERASTICK® (aminolevulinic acid HCl) for Topical Solution, 20%, contains the hydrochloride salt of aminolevulinic acid (ALA), an endogenous 5-carbon aminoketone.

Aminolevulinic acid HCl (ALA HCl) is a white to off-white, odorless crystalline solid that is very soluble in water, slightly soluble in methanol and ethanol, and practically insoluble in chloroform, hexane and mineral oil.

The chemical name for ALA HCl is 5-amino-4-oxopentanoic acid hydrochloride (MW = 167.59). The structural formula is represented below:

The LEVULAN KERASTICK for Topical Solution applicator is a two component system consisting of a plastic tube containing two sealed glass ampules and an applicator tip. One ampule contains 1.5 mL of solution vehicle comprising alcohol USP (ethanol content = 48% v/v), water, laureth-4, isopropyl alcohol, and polyethylene glycol. The other ampule contains 354 mg of ALA HCl as a dry solid. The applicator tube is enclosed in a protective cardboard sleeve and cap. The 20% topical solution is prepared just prior to the time of use by breaking the ampules and mixing the contents by shaking the LEVULAN KERASTICK applicator. The term “ALA HCl” refers to unformulated active ingredient, “LEVULAN KERASTICK for Topical Solution” refers to the drug product in its unmixed state, “LEVULAN KERASTICK Topical Solution” refers to the mixed drug product (in the applicator tube or after application), and “LEVULAN KERASTICK” refers to the applicator only.

CLINICAL PHARMACOLOGY

Pharmacology

The metabolism of aminolevulinic acid (ALA) is the first step in the biochemical pathway resulting in heme synthesis. Aminolevulinic acid is not a photosensitizer, but rather a metabolic precursor of protoporphyrin IX (PpIX), which is a photosensitizer. The synthesis of ALA is normally tightly controlled by feedback inhibition of the enzyme, ALA synthetase, presumably by intracellular heme levels. ALA, when provided to the cell, bypasses this control point and results in the accumulation of PpIX, which is converted into heme by ferrochelatase through the addition of iron to the PpIX nucleus.

According to the presumed mechanism of action, photosensitization following application of LEVULAN KERASTICK Topical Solution occurs through the metabolic conversion of ALA to PpIX, which accumulates in the skin to which LEVULAN Topical Solution has been applied. When exposed to light of appropriate wavelength and energy, the accumulated PpIX produces a photodynamic reaction, a cytotoxic process dependent upon the simultaneous presence of light and oxygen. The absorption of light results in an excited state of the porphyrin molecule, and subsequent spin transfer from PpIX to molecular oxygen generates singlet oxygen, which can further react to form superoxide and hydroxyl radicals. Photosensitization of actinic (solar) keratosis lesions using the LEVULAN KERASTICK, plus illumination with the BLU-U® Blue Light Photodynamic Therapy Illuminator (BLU-U), is the basis for LEVULAN photodynamic therapy (PDT).

Pharmacokinetics

In a human pharmacokinetic study (N=6) using a 128 mg dose of sterile intravenous ALA HCl and oral ALA HCl (equivalent to 100 mg ALA) in which plasma ALA and PpIX were measured, the mean half-life of ALA was 0.70 ± 0.18 h after the oral dose and 0.83 ± 0.05 h after the intravenous dose. The oral bioavailability of ALA was 50-60% with a mean Cmax of 4.65 ± 0.94 µg/mL. PpIX concentrations were low and were detectable only in 42% of the plasma samples. PpIX concentrations in plasma were quite low relative to ALA plasma concentrations, and were below the level of detection (10 ng/mL) after 10 to 12 hours.

ALA does not exhibit fluorescence, while PpIX has a high fluorescence yield. Time-dependent changes in surface fluorescence have been used to determine PpIX accumulation and clearance in actinic keratosis lesions and perilesional skin after application of LEVULAN KERASTICK Topical Solution in 12 patients. Peak fluorescence intensity was reached in 11 ± 1 h in actinic keratoses and 12 ± 1 h in perilesional skin. The mean clearance half-life of fluorescence for lesions was 30 ± 10 h and 28 ± 6 h for perilesional skin. The fluorescence in perilesional skin was similar to that in actinic keratoses. Therefore, LEVULAN KERASTICK Topical Solution should only be applied to the affected skin.

Clinical Studies

LEVULAN KERASTICK for Topical Solution, 20%, plus blue light at 6-10.9 J/cm2, has been used to treat actinic keratoses in 232 patients in six clinical trials. Phase 3 studies were two, identically designed, multicenter, two-arm studies using LEVULAN KERASTICK for Topical Solution applicators plus illumination from the BLU-U for 1000 seconds (16 min 40 sec) for a nominal exposure of 10 J/cm2. Patients were excluded from these studies who had a history of cutaneous photosensitization, porphyria, hypersensitivity to porphyrins, photodermatosis, or inherited or acquired coagulation defects. A minimum of 4 and a maximum of 15 clinically typical, discrete, (Grade 1 or 2, see table 2 for definition), target actinic keratosis lesions were identified. Target lesions on the face or on the scalp, but not in both locations in the same patient, received treatment. The patients were randomized to receive treatment either with the LEVULAN KERASTICK Topical Solution plus BLU-U or vehicle plus BLU-U. Patients were randomized at a 3 to 1 LEVULAN to vehicle ratio. A total of 243 patients were enrolled in two Phase 3 studies (ALA-018, ALA-019). Lesions were designated as cleared (complete response) if the lesion had completely cleared and adherent scaling plaques of actinic keratoses were no longer evident on the surface of the treated skin when palpated. The percentage of patients in whom 75% or more of treated lesions were cleared, and the percentage of patients in whom 100% of treated lesions were cleared (Complete Responders), for each study at 8 weeks after treatment are shown in Table 1.

TABLE 1 Patient Responses at Week 8
 | ALA-018 |  | ALA-019
 | LEVULAN | Vehicle | LEVULAN | Vehicle
 | Patients with > 75% of AK Lesions Cleared
Total No. Patients | 68/87 (78%) | 6/29 (21%) | 71/93 (76%) | 8/32 (25%)
Patients with Face Lesions | 57/71 (80%) | 2/21 (10%) | 57/67 (85%) | 7/19 (37%)
Patients with Scalp Lesions | 11/16 (69%) | 4/8 (50%) | 14/26 (54%) | 1/13 (8%)
 | Complete Responders
Total No. Patients | 60/87 (69%) | 4/29 (14%) | 59/93 (63%) | 4/32 (13%)
Patients with Face Lesions | 49/71 (69%) | 2/21 (10%) | 47/67 (70%) | 4/19 (21%)
Patients with Scalp Lesions | 11/16 (69%) | 2/8 (25%) | 12/26 (46%) | 0/13 (0%)

Because clinical studies ALA-018 and ALA-019 had identical protocols, the combined results from the two trials are shown in the following tables. For actinic keratoses with a variety of thicknesses (excluding very thick, Grade 3 actinic keratoses which were not studied in the phase 3 trials), LEVULAN KERASTICK Topical Solution plus BLU-U is more effective than vehicle plus BLU-U, but as shown in Table 2, the percentage of lesions with complete responses at 8 weeks after treatment with LEVULAN KERASTICK Topical Solution plus blue light illumination was lower for those lesions that were thicker at baseline. Efficacy of LEVULAN KERASTICK Topical Solution plus BLU-U on higher grade lesions was not studied in the Phase 3 clinical efficacy trials.

TABLE 2 Lesions Complete Responses at Week 8 for Different Lesion Grades
 | LEVULAN | Vehicle
Lesion Grade 1 (Slightly palpable actinic keratoses: better felt than seen) | 666/756 (88%) | 122/302 (40%)
Lesion Grade 2 (Moderately thick actinic keratoses: easily seen and felt) | 495/632 (78%) | 52/199 (26%)
Lesion Grade 3 (Very Thick and/or hyperkeratotic actinic keratoses) | 0 | 0

Those patients who were not Complete Responders at week 8 had retreatment of the persistent target lesions at week 8. Among the patients undergoing retreatment, efficacy results seen at 12 weeks after the initial treatment, i.e., at 4 weeks after the second treatment, are shown in Table 3.

TABLE 3 Complete Responders at Week 12, among Patients Receiving Two Treatments
 | LEVULAN | Vehicle
Total No. Patients | 24/56 (43%) | 2/49 (4%)
Patients with Face Lesions | 21/40 (53%) | 2/31 (6%)
Patients with Scalp Lesions | 3/16 (19%) | 0/18 (0%)

The efficacy results seen at 12 weeks after treatment, which include the results at 12 weeks for those patients who received a single treatment as well as the results at 12 weeks for those patients who received a second treatment at week 8, are shown in Table 4.

TABLE 4 Patient Responses at Week 12, among Patients who Received One or Two Treatments
 | LEVULAN | Vehicle
 | Patients with > 75% of AK Lesions Cleared
Total No. Patients | 158/180 (88%) | 12/61 (20%)
Patients with Face Lesions | 127/138 (92%) | 8/40 (20%)
Patients with Scalp Lesions | 31/42 (74%) | 4/21 (19%)
 | Complete Responders
Total No. Patients | 129/180 (72%) | 7/61 (11%)
Patients with Face Lesions | 108/138 (78%) | 5/40 (13%)
Patients with Scalp Lesions | 21/42 (50%) | 2/21 (10%)

Among Complete Responders at week 8, 93% (in study ALA-018) and 83% (in study ALA-019) maintained complete response at week 12. Among patients with scalp lesions, the percentage of patients with 100% of AK lesions having complete response declined from week 8 (55%) to week 12 (50%), because there were more patients with scalp lesions with 100% of AK lesions cleared at week 8 who had a recurrence of a lesion by week 12 than there were patients with scalp lesions who had retreatment of persistent lesions at week 8 and who then achieved 100% of AK lesions cleared by week 12. Patients did not receive follow-up past 12 weeks after the initial treatment.

Patient outcomes recorded in the two Phase 3 trials are depicted in the following flowchart, in which Complete Responders are designated clear. Seven patients in the active treatment arm and three patients in the vehicle treatment arm withdrew or were lost to follow-up, and their outcomes are not included in the flowchart. Three patients in the active treatment arm were treated at baseline but did not return for evaluation until week 12. One patient in the active treatment arm and two in the vehicle treatment arm who were not clear at week 8 did not receive retreatment.

INDICATIONS AND USAGE

The LEVULAN KERASTICK for Topical Solution plus blue light illumination using the BLU-U Blue Light Photodynamic Therapy Illuminator is indicated for the treatment of minimally to moderately thick actinic keratoses (Grade 1 or 2, see table 2 for definition) of the face or scalp.

CONTRAINDICATIONS

The LEVULAN KERASTICK for Topical Solution plus blue light illumination using the BLU-U Blue Light Photodynamic Therapy Illuminator is contraindicated in patients with cutaneous photosensitivity at wavelengths of 400-450 nm, porphyria or known allergies to porphyrins, and in patients with known sensitivity to any of the components of the LEVULAN KERASTICK for Topical Solution.

WARNINGS

The LEVULAN KERASTICK for Topical Solution contains alcohol and is intended for topical use only. Do not apply to the eyes or to mucous membranes. Excessive irritation may be experienced if this product is applied under occlusion.

PRECAUTIONS

General

During the time period between the application of LEVULAN KERASTICK Topical Solution and exposure to activating light from the BLU-U Blue Light Photodynamic Therapy Illuminator, the treatment site will become photosensitive. After LEVULAN KERASTICK Topical Solution application, patients should avoid exposure of the photosensitive treatment sites to sunlight or bright indoor light (e.g., examination lamps, operating room lamps, tanning beds, or lights at close proximity) during the period prior to blue light treatment. Exposure may result in a stinging and/or burning sensation and may cause erythema and/or edema of the lesions. Before exposure to sunlight, patients should, therefore, protect treated lesions from the sun by wearing a wide-brimmed hat or similar head covering of light-opaque material. Sunscreens will not protect against photosensitivity reactions caused by visible light. It has not been determined if perspiration can spread the LEVULAN KERASTICK Topical Solution outside the treatment site to eye or surrounding skin.

Application of LEVULAN KERASTICK Topical Solution to perilesional areas of photodamaged skin of the face or scalp may result in photosensitization. Upon exposure to activating light from the BLU-U Blue Light Photodynamic Therapy Illuminator, such photosensitized skin may produce a stinging and/or burning sensation and may become erythematous and/or edematous in a manner similar to that of actinic keratoses treated with LEVULAN PDT. Because of the potential for skin to become photosensitized, the LEVULAN KERASTICK for Topical Solution should be used by a qualified health professional to apply drug only to actinic keratoses and not perilesional skin.

The LEVULAN KERASTICK for Topical Solution has not been tested on patients with inherited or acquired coagulation defects.

Information for Patients

LEVULAN Photodynamic Therapy for Actinic Keratoses.

The first step in LEVULAN KERASTICK photodynamic therapy (PDT) for actinic keratoses is application of the LEVULAN KERASTICK Topical Solution to actinic keratoses located on the patient’s face or scalp. After LEVULAN KERASTICK Topical Solution is applied to the actinic keratoses in the doctor’s office, the patient will be told to return the next day. During this time the actinic keratoses will become sensitive to light (photosensitive). Care should be taken to keep the treated actinic keratoses dry and out of bright light. After LEVULAN KERASTICK Topical Solution is applied, it is important for the patient to wear light-protective clothing, such as a wide-brimmed hat, when exposed to sunlight or sources of light. Fourteen to eighteen hours after application of LEVULAN KERASTICK Topical Solution the patient will return to the doctor’s office to receive blue light treatment, which is the second and final step in the treatment. Prior to blue light treatment, the actinic keratoses will be rinsed with tap water. The patient will be given goggles to wear as eye protection during the blue light treatment. The blue light is of low intensity and will not heat the skin. However, during the light treatment, which lasts for approximately 17 minutes, the patient will experience sensations of tingling, stinging, prickling or burning of the treated lesions. These feelings of discomfort should improve at the end of the light treatment. Following treatment, the actinic keratoses and, to some degree, the surrounding skin, will redden, and swelling and scaling may also occur. However, these lesion changes are temporary and should completely resolve by 4 weeks after treatment.

Photosensitivity

After LEVULAN KERASTICK Topical Solution is applied to the actinic keratoses in the doctor’s office, the patient should avoid exposure of the photosensitive actinic keratoses to sunlight or bright indoor light (e.g., from examination lamps, operating room lamps, tanning beds, or lights at close proximity) during the period prior to blue light treatment. If the patient feels stinging and/or burning on the actinic keratoses, exposure to light should be reduced. Before going into sunlight, the patient should protect treated lesions from the sun by wearing a wide-brimmed hat or similar head covering of light-opaque material. Sunscreens will not protect the patient against photosensitivity reactions.

If for any reason the patient cannot return for blue light treatment during the prescribed period after application of LEVULAN KERASTICK Topical Solution (14 to 18 hours), the patient should call the doctor. The patient should also continue to avoid exposure of the photosensitized lesions to sunlight or prolonged or intense light for at least 40 hours. If stinging and/or burning is noted, exposure to light should be reduced.

Drug Interactions

There have been no formal studies of the interaction of LEVULAN KERASTICK for Topical Solution with any other drugs, and no drug-specific interactions were noted during any of the controlled clinical trials. It is, however, possible that concomitant use of other known photosensitizing agents such as griseofulvin, thiazide diuretics, sulfonylureas, phenothiazines, sulfonamides and tetracyclines might increase the photosensitivity reaction of actinic keratoses treated with the LEVULAN KERASTICK for Topical Solution.

Carcinogenesis, Mutagenesis, Impairment to Fertility

No carcinogenicity testing has been carried out using ALA. No evidence of mutagenic effects was seen in four studies conducted with ALA to evaluate this potential. In the Salmonella-Escherichia coli/mammalian microsome reverse mutation assay (Ames mutagenicity assay), no increases in the number of revertants were observed with any of the tester strains. In the Salmonella-Escherichia coli/mammalian microsome reverse mutation assay in the presence of solar light radiation (Ames mutagenicity assay with light), ALA did not cause an increase in the number of revertants per plate of any of the tester strains in the presence or absence of simulated solar light. In the L5178Y TK± mouse lymphoma forward mutation assay, ALA was evaluated as negative with and without metabolic activation under the study conditions. PpIX formation was not demonstrated in any of these in vitro studies. In the in vivo mouse micronucleus assay, ALA was considered negative under the study exposure conditions. In contrast, at least one report in the literature has noted genotoxic effects in cultured rat hepatocytes after ALA exposure with PpIX formation. Other studies have documented oxidative DNA damage in vivo and in vitro as a result of ALA exposure.

No assessment of effects of ALA HCl on fertility has been performed in laboratory animals. It is unknown what effects systemic exposure to ALA HCl might have on fertility or reproductive function.

Pregnancy Category C

Animal reproduction studies have not been conducted with ALA HCl. It is also not known whether LEVULAN KERASTICK Topical Solution can cause fetal harm when administered to a pregnant woman or can affect reproductive capacity. LEVULAN KERASTICK Topical Solution should be given to a pregnant woman only if clearly needed.

Nursing Mothers

The levels of ALA or its metabolites in the milk of subjects treated with LEVULAN KERASTICK Topical Solution have not been measured. Because many drugs are excreted in human milk, caution should be exercised when LEVULAN KERASTICK Topical Solution is administered to a nursing woman.

ADVERSE REACTIONS

In Phase 3 studies, no non-cutaneous adverse events were found to be consistently associated with LEVULAN KERASTICK Topical Solution application followed by blue light exposure.

Photodynamic Therapy Response

The constellation of transient local symptoms of stinging and/or burning, itching, erythema and edema as a result of LEVULAN KERASTICK Topical Solution plus BLU-U treatment was observed in all clinical studies of LEVULAN KERASTICK for Topical Solution Photodynamic Therapy for actinic keratoses treatment. Stinging and/or burning subsided between 1 minute and 24 hours after the BLU-U Blue Light Photodynamic Therapy Illuminator was turned off, and appeared qualitatively similar to that perceived by patients with erythropoietic protoporphyria upon exposure to sunlight. There was no clear drug dose or light dose dependent change in the incidence or severity of stinging and/or burning.

In two Phase 3 trials, the sensation of stinging and/or burning appeared to reach a plateau at 6 minutes into the treatment. Severe stinging and/or burning at one or more lesions being treated was reported by at least 50% of the patients at some time during treatment. The majority of patients reported that all lesions treated exhibited at least slight stinging and/or burning. Less than 3% of patients discontinued light treatment due to stinging and/or burning.

The most common changes in lesion appearance after LEVULAN KERASTICK Topical Solution Photodynamic Therapy were erythema and edema. In 99% of active treatment patients, some or all lesions were erythematous shortly after treatment, while in 79% of vehicle treatment patients, some or all lesions were erythematous. In 35% of active treatment patients, some or all lesions were edematous, while no vehicle-treated patients had edematous lesions. Both erythema and edema resolved to baseline or improved by 4 weeks after therapy. LEVULAN KERASTICK Topical Solution application to photodamaged perilesional skin resulted in photosensitization of photodamaged skin and in a photodynamic response. (see Precautions).

Other Localized Cutaneous Adverse Experiences

Table 5 depicts the incidence and severity of cutaneous adverse events, stratified by anatomic site treated.

TABLE 5 Post-PDT Cutaneous Adverse Events - ALA-018/ALA-019
 | FACE |  |  |  | SCALP
 | LEVULAN (n=139) |  | Vehicle (n=41) |  | LEVULAN (n=42) |  | Vehicle (n=21)
Degree of Severity | Mild/ Moderate | Severe | Mild/ Moderate | Severe | Mild/ Moderate | Severe | Mild/ Moderate | Severe
Scaling/Crusting | 71% | 1% | 12% | 0% | 64% | 2% | 19% | 0%
Pain | 1% | 0% | 0% | 0% | 0% | 0% | 0% | 0%
Tenderness | 1% | 0% | 0% | 0% | 2% | 0% | 0% | 0%
Itching | 25% | 1% | 7% | 0% | 14% | 7% | 19% | 0%
Edema | 1% | 0% | 0% | 0% | 0% | 0% | 0% | 0%
Ulceration | 4% | 0% | 0% | 0% | 2% | 0% | 0% | 0%
Bleeding/Hemorrhage | 4% | 0% | 0% | 0% | 2% | 0% | 0% | 0%
Hypo/hyper-pigmentation | 22% |  | 20% |  | 36% |  | 33%
Vesiculation | 4% | 0% | 0% | 0% | 5% | 0% | 0% | 0%
Pustules | 4% | 0% | 0% | 0% | 0% | 0% | 0% | 0%
Oozing | 1% | 0% | 0% | 0% | 0% | 0% | 0% | 0%
Dysesthesia | 2% | 0% | 0% | 0% | 0% | 0% | 0% | 0%
Scabbing | 2% | 1% | 0% | 0% | 0% | 0% | 0% | 0%
Erosion | 14% | 1% | 0% | 0% | 2% | 0% | 0% | 0%
Excoriation | 1% | 0% | 0% | 0% | 0% | 0% | 0% | 0%
Wheal/Flare | 7% | 1% | 0% | 0% | 2% | 0% | 0% | 0%
Skin disorder NOS | 5% | 0% | 0% | 0% | 12% | 0% | 5% | 0%

Adverse Experiences Reported by Body System

In the Phase 3 studies, 7 patients experienced a serious adverse event. All were deemed remotely or not related to treatment. No clinically significant patterns of clinical laboratory changes were observed for standard serum chemical or hematologic parameters in any of the controlled clinical trials.

OVERDOSAGE

LEVULAN KERASTICK Topical Solution overdose have not been reported. In the unlikely event that the drug is ingested, monitoring and supportive care are recommended. The patient should be advised to avoid incidental exposure to intense light sources for at least 40 hours. The consequences of exceeding the recommended topical dosage are unknown.

BLU-U® Light Overdose

There is no information on overdose of blue light from the BLU-U Blue Light Photodynamic Therapy Illuminator following LEVULAN KERASTICK Topical Solution application.

DOSAGE AND ADMINISTRATION

LEVULAN KERASTICK for Topical Solution 20% is intended for direct application to individual lesions diagnosed as actinic keratoses and not to perilesional skin. This product is not intended for application by patients or unqualified medical personnel. Application should involve either scalp or face lesions, but not both simultaneously. The recommended treatment frequency is: one application of the LEVULAN KERASTICK Topical Solution and one dose of illumination per treatment site per 8-week treatment session. Each individual LEVULAN KERASTICK should be used for only one patient. Photodynamic therapy for actinic keratoses with LEVULAN KERASTICK for Topical Solution is a two stage process involving a) application of the product to the target lesions with LEVULAN KERASTICK Topical Solution, followed 14 to 18 hours later by b) illumination with blue light using the BLU-U Blue Light Photodynamic Therapy Illuminator. The second visit, for illumination, must take place in the 14-18 hour window following application. Patients in clinical trials usually received application in the late afternoon, with illumination the following morning.

TABLE 6 Schedule for LEVULAN and Blue Light Administration
LEVULAN KERASTICK Topical Solution Application | Time Window for Blue Light Illumination
6 am | 8 pm to Midnight
7 am | 9 pm to 1 am
8 am | 10 pm to 2 am
9 am | 11 pm to 3 am
10 am | Midnight to 4 am
11 am | 1 am to 5 am
12 pm | 2 am to 6 am
1 pm | 3 am to 7 am
2 pm | 4 am to 8 am
3 pm | 5 am to 9 am
4 pm | 6 am to 10 am
5 pm | 7 am to 11 am
6 pm | 8 am to Noon
7 pm | 9 am to 1 pm
8 pm | 10 am to 2 pm
9 pm | 11 am to 3 pm
10 pm | Noon to 4 pm

Treated lesions that have not completely resolved after 8 weeks may be treated a second time with LEVULAN KERASTICK for Topical Solution Photodynamic Therapy. Patients did not receive follow-up past 12 weeks after the initial treatment, so the incidence of recurrence of treated lesions past 12 weeks and the role of further treatment is not known.

Step A - LEVULAN KERASTICK for Topical Solution Application

Actinic keratoses targeted for treatment should be clean and dry prior to application of LEVULAN KERASTICK for Topical Solution.

Preparation:

The LEVULAN KERASTICK Topical Solution should be prepared as follows:

1. Hold the LEVULAN KERASTICK so that the applicator cap is pointing up. | 2. Crush the bottom ampule containing the solution vehicle by applying finger pressure to Position A on the cardboard sleeve.
3. Crush the top ampule containing the ALA HCl powder by applying finger pressure to Position B on the cardboard sleeve. NOTE: To ensure both ampules are crushed continue crushing the applicator downward, applying finger pressure to Position A. | 4. Holding the LEVULAN KERASTICK between the thumb and forefinger, point the applicator cap away from the face, shake the LEVULAN KERASTICK gently for at least 3 minutes to completely dissolve the drug powder in the solution vehicle. Do not press on the end cap while shaking.

LEVULAN KERASTICK Preparation: Following solution admixture, remove the cap from the LEVULAN KERASTICK. The dry applicator tip should be dabbed on a gauze pad until uniformly wet with solution.

Application:

Apply the solution directly to the target lesions by dabbing gently with the wet applicator tip. Enough solution should be applied to uniformly wet the lesion surface, including the edges without excess running or dripping. The effect of LEVULAN KERASTICK Topical Solution on ocular tissues is unknown. LEVULAN KERASTICK Topical Solution should not be applied to the periorbital area or allowed to contact ocular or mucosal surfaces. Once the initial application has dried, apply again in the same manner. The LEVULAN KERASTICK Topical Solution must be used immediately following preparation (dissolution) due to the instability of the activated product. If the solution application is not completed within 2 hours of activation, the applicator should be discarded and a new LEVULAN KERASTICK for Topical Solution used.

Photosensitization of the treated lesions will take place over the next 14-18 hours. The actinic keratoses should not be washed during this time. The patient should be advised to wear a wide-brimmed hat or other protective apparel to shade the treated actinic keratosis lesions from sunlight or other bright light sources until BLU-U treatment. The patient should be advised to reduce light exposure if the sensations of stinging and/or burning are experienced.

If for any reason the patient cannot be given BLU-U treatment during the prescribed time after LEVULAN KERASTICK Topical Solution application, he or she may nonetheless experience sensations of stinging and/or burning if the photosensitized actinic keratoses are exposed to sunlight or prolonged or intense light at that time. The patient should be advised to wear a wide-brimmed hat or other protective apparel to shade the treated actinic keratosis lesions from sunlight or other bright light sources until at least 40 hours after the application of LEVULAN KERASTICK Topical Solution. The patient should be advised to reduce light exposure if the sensations of stinging and/or burning are experienced.

Step B - Administration of BLU-U Treatment 14 to 18 hours after application of LEVULAN KERASTICK Topical Solution

At the visit for light illumination, the actinic keratoses to be treated should be gently rinsed with water and patted dry. Photoactivation of actinic keratoses treated with LEVULAN KERASTICK Topical Solution is accomplished with BLU-U illumination from the BLU-U Blue Light Photodynamic Therapy Illuminator. A 1000 second (16 minutes 40 seconds) exposure is required to provide a 10 J/cm2 light dose. During light treatment, both patients and medical personnel should be provided with blue blocking protective eyewear, as specified In the BLU-U Operating Instructions, to minimize ocular exposure. Please refer to the BLU-U Operating Instructions for further information on conducting the light treatment. Patients should be advised that transient stinging and/or burning at the target lesion sites occurs during the period of light exposure.

If blue light treatment with the BLU-U Blue Light Photodynamic Therapy Illuminator is interrupted or stopped for any reason, it should not be restarted and the patient should be advised to protect the treated lesions from exposure to sunlight or prolonged or intense light for at least 40 hours after application of the LEVULAN KERASTICK Topical Solution from the first visit.

For patients with facial lesions:

1. The BLU-U Blue Light Photodynamic Therapy Illuminator is positioned so that the base is slightly above the patient’s shoulder, parallel to the patient’s face.
2. The BLU-U is positioned around the patient’s head so the entire surface area to be treated lies between 2” and 4” from the BLU-U surface:
  a) The patient’s nose should be no closer than 2” from the surface;
  b) The patient’s forehead and cheeks should be no further than 4” from the surface;
  c) The sides of the patient’s face and the patient’s ears should be no closer than 2” from the BLU-U surface.

A Chin Rest, available from DUSA Pharmaceuticals, Inc., may be used to provide support for the patient’s head during treatment.

For patients with scalp lesions:

1. The knobs on either side of the BLU-U are loosened and the BLU-U is rotated to a horizontal position.
2. The BLU-U is positioned around the patient’s head so the entire surface area to be treated lies between 2” and 4” from the BLU-U surface:
  a) The patient’s scalp should be no closer than 2” from the surface;
  b) The patient’s scalp should be no further than 4” from the surface;
  c) The sides of the patient’s face and the patient’s ears should be no closer than 2” from the BLU-U surface.

A Chin Rest, available from DUSA Pharmaceuticals, Inc., may be used to provide support for the patient’s head during treatment.

LEVULAN KERASTICK for Topical Solution is not intended for use with any device other than the BLU-U Blue Light Photodynamic Therapy Illuminator. Use of LEVULAN KERASTICK for Topical Solution without subsequent BLU-U illumination is not recommended.

HOW SUPPLIED

The LEVULAN KERASTICK for Topical Solution, 20%, is a single-unit dosage form, supplied in packs of 6. Each LEVULAN KERASTICK for Topical Solution applicator consists of a plastic tube containing two sealed glass ampules and an applicator tip. One ampule contains 1.5 mL of solution vehicle. The other ampule contains 354 mg of aminolevulinic acid HCl. The applicator is covered with a protective cardboard sleeve and cap.

Product Package | NDC number
Individual LEVULAN KERASTICK for Topical Solution, 20% | 67308-101-01
Carton of 6 LEVULAN KERASTICKS for Topical Solution, 20% | 67308-101-06

Storage Conditions: Store between 20° - 25 °C (68° - 77 °F); excursions permitted to 15°- 30 °C (59° - 86 °F) [See USP Controlled Room Temperature]. The LEVULAN KERASTICK for Topical Solution should be used immediately following preparation (dissolution). Solution application must be completed within 2 hours of preparation. An applicator that has been prepared must be discarded 2 hours after mixing (dissolving) and a new LEVULAN KERASTICK for Topical Solution used, if needed.

Rx

LEVULAN®, KERASTICK®, BLU-U®, DUSA Pharmaceuticals, Inc.® and DUSA® are registered trademarks of DUSA Pharmaceuticals, Inc.®

US Patents: 5,079,262, 5,211,938, 5,422,093, 5,954,703, 6,710,066

Manufactured for: | DUSA Pharmaceuticals, Inc.® 25 Upton Drive Wilmington MA 01887
Revision: F | LAB-0530

For more information please contact:

1-877-533-3872

or

1-978-657-7500

www.dusapharma.com